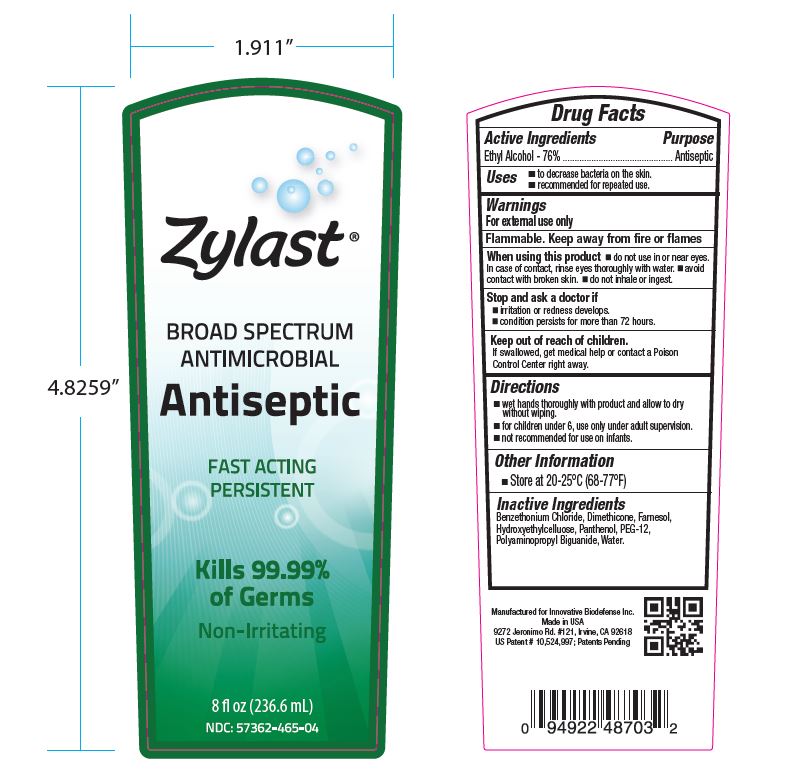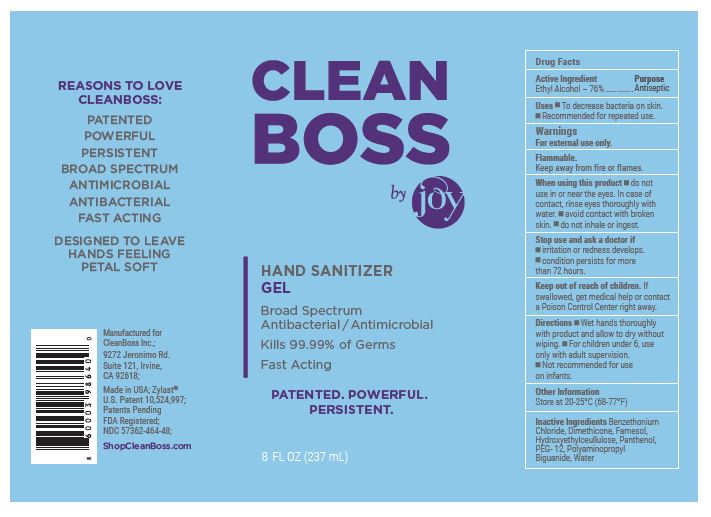 DRUG LABEL: Zylast Antiseptic
NDC: 57362-465 | Form: GEL
Manufacturer: Innovative BioDefense
Category: otc | Type: HUMAN OTC DRUG LABEL
Date: 20200826

ACTIVE INGREDIENTS: ALCOHOL 44.9 mL/59.1 mL
INACTIVE INGREDIENTS: WATER

Antiseptic 8oz
Drug Facts

ACTIVE INGREDIENT

Ethyl Alcohol - 76%

PURPOSE

Antiseptic

INDICATIONS AND USAGE

- To decrease bacteria on skin.
- Recommened for repeated use.

ASK DOCTOR

Discontinue use if irritation and redness develops. Consult a doctor if condition persists for more than 72 hours.

WARNINGS

- For external use only.
- Flammable. Keep away from fire or flames

- Do not use in or near eyes. In case of contact, rinse eyes thoroughly with water.
- Avoid contact with broken skin.
- Do not inhale or ingest.

KEEP OUT OF REACH OF CHILDREN

If swallowed, get medical help or contact Poison Control center right away.

DOSAGE AND ADMINISTRATION

- Wet hands thoroughly with product and allow to dry without wiping.
- For children under 6, use only with adult supervision.
- Not recommended for use on infants.

STORAGE AND HANDLING

- Store at 20-25 degrees Celsius (68-77 degrees Farenheit)

INACTIVE INGREDIENT

Water, Polyaminopropyl Biguanide, Panthenol, Hydroxyethylcellulose, Farnesol, PEG-12, Dimethicone, Benzethonium Chloride

RECENT MAJOR CHANGES

1. Indications and Usage
2. Warnings and Precaution
3. Dosage and Administration
4. When Using This Product
5. Order of Sections

PACKAGE LABEL

NDC 57362-465-04

Zylast Antiseptic 8oz

Broad Spectrum

Antimicrobial

Non-Irritating

NDC: 57362-465-48